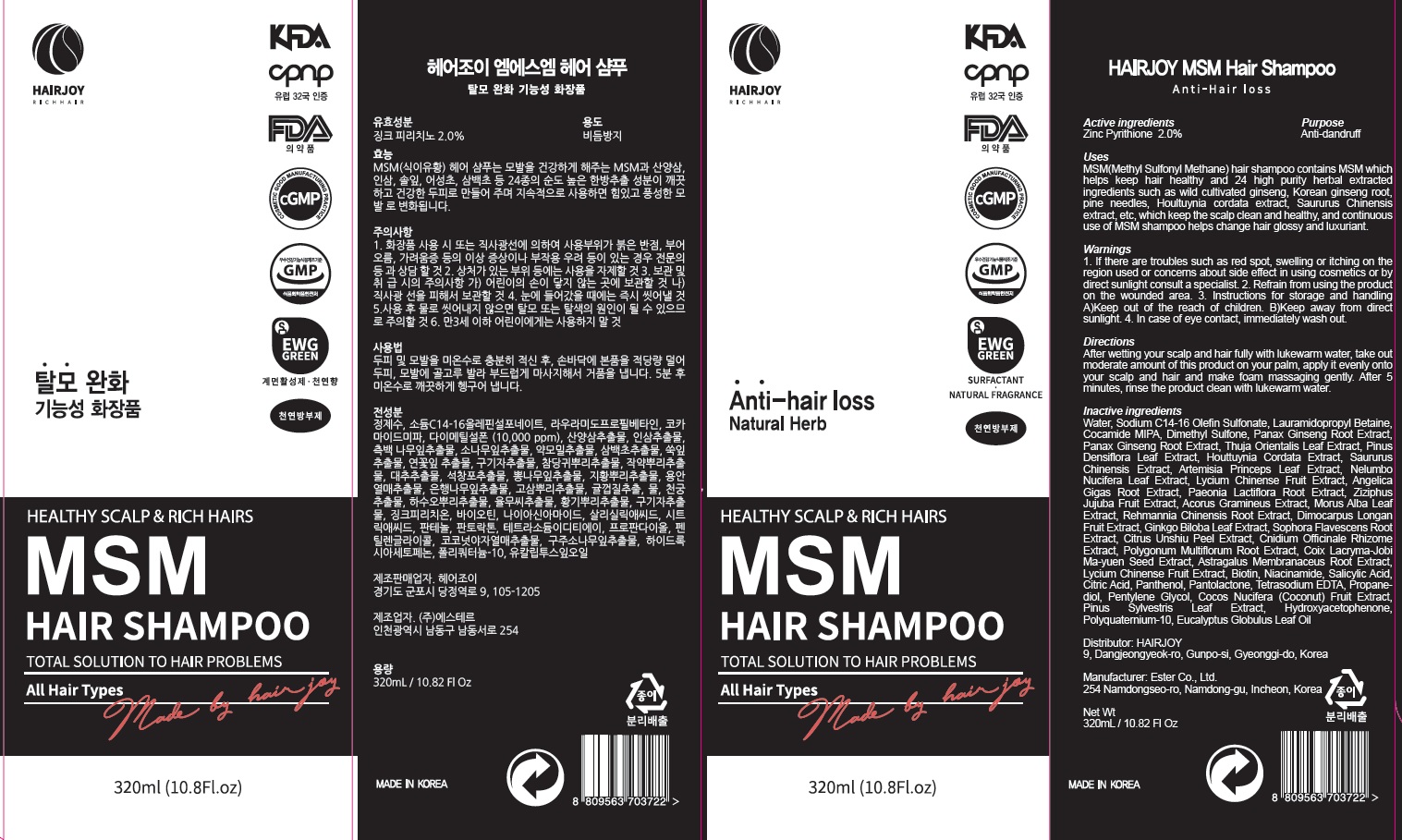 DRUG LABEL: HAIRJOY MSM HAIR
NDC: 69384-040 | Form: SHAMPOO
Manufacturer: HAIRJOY
Category: otc | Type: HUMAN OTC DRUG LABEL
Date: 20191205

ACTIVE INGREDIENTS: PYRITHIONE ZINC 6.4 g/320 mL
INACTIVE INGREDIENTS: Water; SODIUM C14-16 OLEFIN SULFONATE

ACTIVE INGREDIENT

Active ingredient: Zinc Pyrithione 2.0%

INACTIVE INGREDIENT

Inactive ingredients:

Water, Sodium C14-16 Olefin Sulfonate, Lauramidopropyl Betaine, Cocamide MIPA, Dimethyl Sulfone, Panax Ginseng Root Extract, Panax Ginseng Root Extract, Thuja Orientalis Leaf Extract, Pinus Densiflora Leaf Extract, Houttuynia Cordata Extract, Saururus Chinensis Extract, Artemisia Princeps Leaf Extract, Nelumbo Nucifera Leaf Extract, Lycium Chinense Fruit Extract, Angelica Gigas Root Extract, Paeonia Lactiflora Root Extract, Ziziphus Jujuba Fruit Extract, Acorus Gramineus Extract, Morus Alba Leaf Extract, Rehmannia Chinensis Root Extract, Dimocarpus Longan Fruit Extract, Ginkgo Biloba Leaf Extract, Sophora Flavescens Root Extract, Citrus Unshiu Peel Extract, Cnidium Officinale Rhizome Extract, Polygonum Multiflorum Root Extract, Coix Lacryma-Jobi Ma-yuen Seed Extract, Astragalus Membranaceus Root Extract, Lycium Chinense Fruit Extract, Biotin, Niacinamide, Salicylic Acid, Citric Acid, Panthenol, Pantolactone, Tetrasodium EDTA, Propanediol, Pentylene Glycol, Cocos Nucifera (Coconut) Fruit Extract, Pinus Sylvestris Leaf Extract, Hydroxyacetophenone, Polyquaternium-10, Eucalyptus Globulus Leaf Oil

PURPOSE

Purpose: Anti-dandruff

WARNINGS

1 . If there are troubles such as red spot, swelling or itching on the region used or concerns about side effect in using cosmetics or by direct sunlight consult a specialist.
2. Refrain from using the product on the wounded area.
3. Instructions for storage and handling A) Keep out of the reach of children. B) Keep away from direct sunlight.
4. In case of eys contact, immediately wash out.

KEEP OUT OF REACH OF CHILDREN

Uses

MSM(Methyl Sulfonyl Methane) hair shampoo contains
MSM which helps keep hair healthy and 24 high purity
herbal extracted ingredients such as wild cultivated ginseng, Korean ginseng root, pine needles, Houltuynia Cordata extract, Saururus Chinensis extract, etc, which keep the scal clean and healthy, and continuous use of MSM shampoo helps change hair glossy and luxuriant.

Directions

After wetting your scalp and hair fully with lukewarm water, take out moderate amount of this product on your palm, apply it evenly onto your scalp and hair and make foam massaging gently. After 5 minutes, rinse the product clean with lukewarm water.